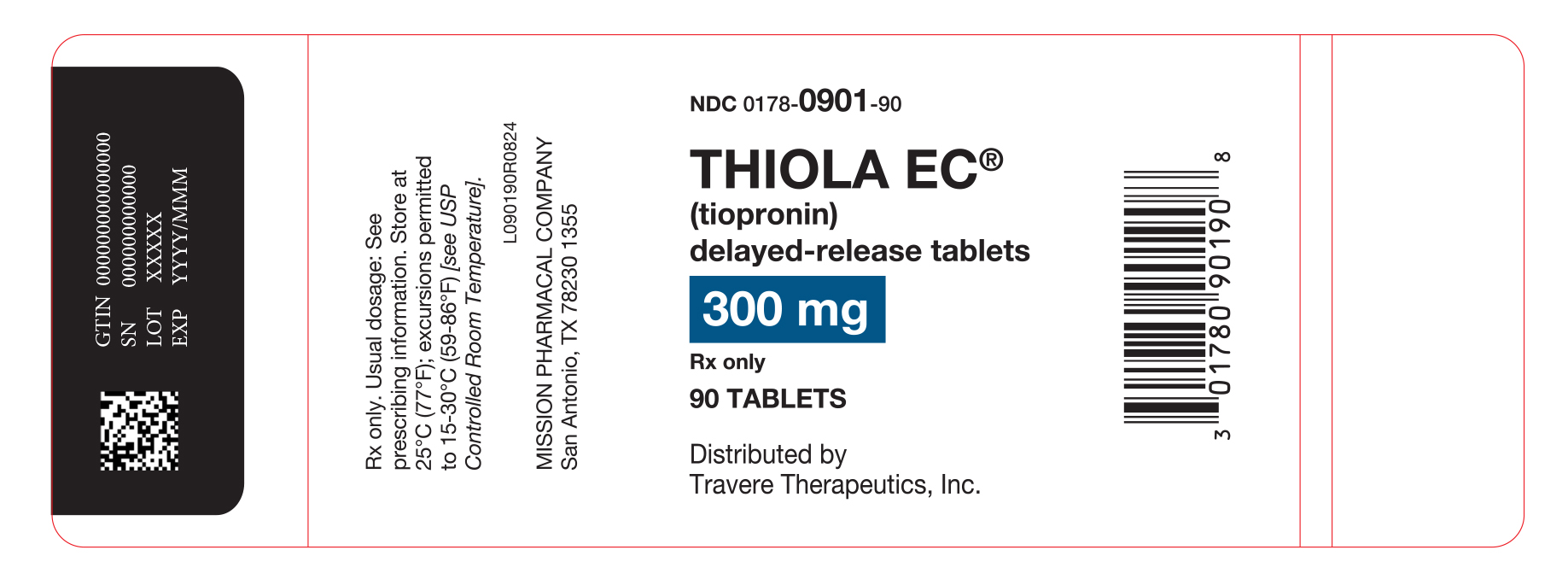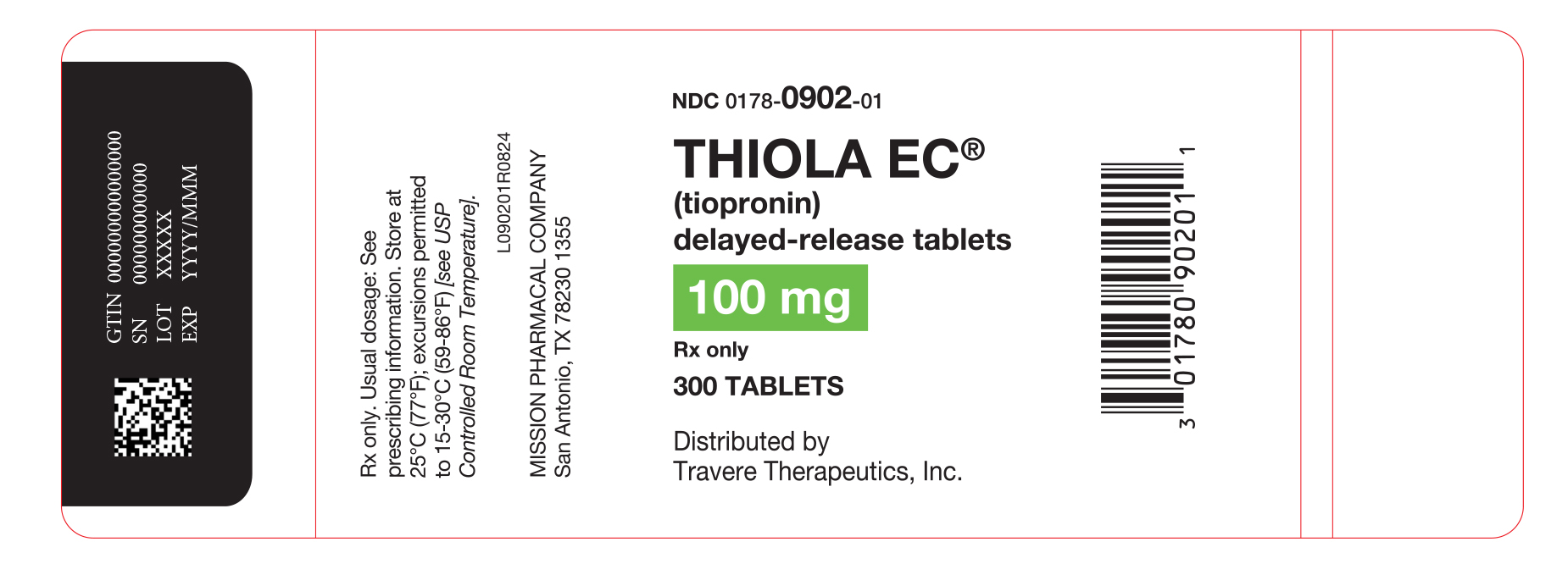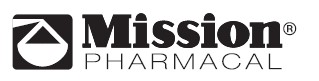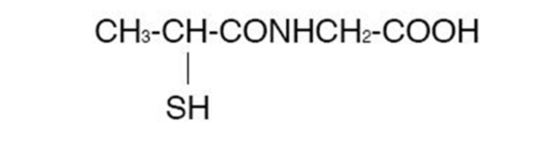 DRUG LABEL: Thiola EC
NDC: 0178-0901 | Form: TABLET, DELAYED RELEASE
Manufacturer: Mission Pharmacal Company
Category: prescription | Type: HUMAN PRESCRIPTION DRUG LABEL
Date: 20251007

ACTIVE INGREDIENTS: TIOPRONIN 300 mg/1 1
INACTIVE INGREDIENTS: LACTOSE MONOHYDRATE; HYDROXYPROPYL CELLULOSE, UNSPECIFIED; HYDROXYPROPYL CELLULOSE, LOW SUBSTITUTED; HYPROMELLOSE, UNSPECIFIED; METHACRYLIC ACID - ETHYL ACRYLATE COPOLYMER (1:1) TYPE A; TALC; TRIETHYL CITRATE; MAGNESIUM STEARATE

HIGHLIGHTS OF PRESCRIBING INFORMATION

These highlights do not include all the information needed to use THIOLA EC®safely and effectively. See full prescribing information for THIOLA EC.
THIOLA EC (tiopronin) delayed-release tablets, for oral use
Initial U.S. Approval: 1988

RECENT MAJOR CHANGES

Dosage and Administration (2.2) | 03/2021

1 INDICATIONS AND USAGE

THIOLA EC is a reducing and complexing thiol indicated, in combination with high fluid intake, alkali, and diet modification, for the prevention of cystine stone formation in adults and pediatric patients 20 kg and greater with severe homozygous cystinuria, who are not responsive to these measures alone. (1)

2 DOSAGE AND ADMINISTRATION

- The recommended initial dosage in adult patients is 800 mg/day. In clinical studies, the average dosage was about 1,000 mg/day. (2.1)
- The recommended initial dosage in pediatric patients 20 kg and greater is 15 mg/kg/day. Avoid dosages greater than 50 mg/kg per day in pediatric patients. (5.1, 8.4)
- Measure urinary cystine 1 month after initiation of THIOLA EC and every 3 months thereafter (2.3)
- Administer THIOLA EC in 3 divided doses at the same times each day, with or without food. Maintain a routine pattern with regard to meals. (2.1)
- THIOLA EC can be crushed and mixed with applesauce. For preparation and administration instructions, see the full prescribing information. (2.2)

3 DOSAGE FORMS AND STRENGTHS

Tablets: 100 mg and 300 mg (3)

4 CONTRAINDICATIONS

- Hypersensitivity to tiopronin or any component of THIOLA EC (4)

5 WARNINGS AND PRECAUTIONS

- Proteinuria, including nephrotic syndrome, and membranous nephropathy, has been reported with tiopronin use. Pediatric patients receiving greater than 50 mg/kg of tiopronin per day may be at increased risk for proteinuria. (2.1, 5.1, 8.4)
- Hypersensitivity reactions have been reported during tiopronin treatment. (4, 5.2)

6 ADVERSE REACTIONS

Most common adverse reactions (≥10%) are nausea, diarrhea or soft stools, oral ulcers, rash, fatigue, fever, arthralgia, proteinuria, and emesis. (6)

To report SUSPECTED ADVERSE REACTIONS, contact Mission Pharmacal Company at toll-free phone # 1-800-298-1087 or FDA at 1-800-FDA-1088 or www.fda.gov/medwatch.

8 USE IN SPECIFIC POPULATIONS

- Lactation: Breastfeeding is not recommended. (8.2)
- Geriatric: Choose dose carefully and monitor renal function in the elderly. (8.5)

FULL PRESCRIBING INFORMATION

1 INDICATIONS AND USAGE

THIOLA EC is indicated, in combination with high fluid intake, alkali, and diet modification, for the prevention of cystine stone formation in adults and pediatric patients 20 kg and greater with severe homozygous cystinuria, who are not responsive to these measures alone.

2 DOSAGE AND ADMINISTRATION

2.1 Recommended Dosage

Adults: The recommended initial dosage in adult patients is 800 mg/day. In clinical studies, the average dosage was about 1,000 mg/day.

Pediatrics: The recommended initial dosage in pediatric patients weighing 20 kg and greater is 15 mg/kg/day. Avoid dosages greater than 50 mg/kg per day in pediatric patients [see Warnings and Precautions (5.1), Use in Specific Populations (8.4)] .

Administer THIOLA EC in 3 divided doses at the same times each day, with or without food. Maintain a routine pattern with regard to meals.

Consider starting THIOLA EC at a lower dosage in patients with history of severe toxicity to d-penicillamine.

2.2 Preparation and Administration Instructions

For patients who cannot swallow the tablet whole, THIOLA EC can be crushed and mixed with applesauce. Administration of THIOLA EC with other liquids or foods has not been studied and is not recommended.

Preparation and Administration of THIOLA EC Mixed in Applesauce
For patients who can swallow semi-solid food, THIOLA EC can be crushed and mixed with applesauce:

1. Crush the THIOLA EC tablet in a clean pill crusher or mortar and pestle. Always crush one tablet at a time.
2. Measure approximately one tablespoon of applesauce and transfer it into a container with the crushed THIOLA EC tablet.
3. Mix the crushed THIOLA EC tablet in the applesauce until the powder is well dispersed.
4. Administer the entire THIOLA EC-applesauce mixture to the patient’s mouth immediately. (However, if this is not possible, the mixture can be stored in a refrigerator for up to 2 hours after adding the crushed tablet to the applesauce. Discard any mixture that has not been given within 2 hours.)
5. To assure that any leftover applesauce mixture from the container is recovered, add tap water to the same container, mix, and have the patient drink the water.

2.3 Monitoring

Measure urinary cystine 1 month after starting THIOLA EC and every 3 months thereafter. Adjust THIOLA EC dosage to maintain urinary cystine concentration less than 250 mg/L.

Assess for proteinuria before treatment and every 3 to 6 months during treatment [see Warnings and Precautions (5.1)] .

Discontinue THIOLA EC in patients who develop proteinuria, and monitor urinary protein and renal function. Consider restarting THIOLA EC treatment at a lower dosage after resolution of proteinuria.

3 DOSAGE FORMS AND STRENGTHS

Tablets for oral use:
100 mg tablets: round, white to off-white and imprinted in red with “T1” on one side
300 mg tablets: round, white to off-white and imprinted in red with “T3” on one side

4 CONTRAINDICATIONS

THIOLA EC is contraindicated in patients with hypersensitivity to tiopronin or any other components of THIOLA EC [see Warnings and Precautions (5.2)] .

5 WARNINGS AND PRECAUTIONS

5.1 Proteinuria

Proteinuria, including nephrotic syndrome, and membranous nephropathy, have been reported with tiopronin use. Pediatric patients receiving greater than 50 mg/kg of tiopronin per day may be at increased risk for proteinuria. [see Dosage and Administration (2.3), Adverse Reactions (6.1, 6.2) Use in Specific Populations (8.4)] . Monitor patients for the development of proteinuria and discontinue therapy in patients who develop proteinuria [see Dosage and Administration (2.3)] .

5.2 Hypersensitivity Reactions

Hypersensitivity reactions (drug fever, rash, fever, arthralgia and lymphadenopathy) have been reported [see Contraindications (4)] .

6 ADVERSE REACTIONS

The following adverse reactions are discussed in greater detail in other sections of the labeling:

- Proteinuria [see Warnings and Precautions (5.1)]
- Hypersensitivity [see Warnings and Precautions (5.2)]

6.1 Clinical Trials Experience

Because clinical trials are conducted under widely varying conditions, the adverse reaction rates observed in the clinical trials of the drug cannot be directly compared to rates in the clinical trials of another drug and may not reflect the rates observed in practice.

Adverse reactions occurring at an incidence of ≥5% in an uncontrolled trial in 66 patients with cystinuria age 9 to 68 years are shown in the table below. Patients in group 1 had previously been treated with d-penicillamine; those in group 2 had not. Of those patients who had stopped taking d-penicillamine due to toxicity (34 out of 49 patients in group 1), 22 were able to continue treatment with THIOLA. In those without prior history of d-penicillamine treatment, 6% developed reactions of sufficient severity to require THIOLA withdrawal.

Table 1presents adverse reactions ≥5% in either treatment group occurring in this trial.

Table 1: | Adverse Reactions Occurring in One or More Patients
System Organ Class |  | Adverse Reaction | Group 1 Previously treated with d‑penicillamine (N = 49) | Group 2 Naïve to d‑penicillamine (N = 17)
Blood and Lymphatic System Disorders |  | anemia | 1 (2%) | 1 (6%)
Gastrointestinal Disorders |  | nausea | 12 (25%) | 2 (12%)
Gastrointestinal Disorders |  | emesis | 5 (10%) | –
Gastrointestinal Disorders |  | diarrhea/soft stools | 9 (18%) | 1 (6%)
Gastrointestinal Disorders |  | abdominal pain | – | 1 (6%)
Gastrointestinal Disorders |  | oral ulcers | 6 (12%) | 3 (18%)
General Disorders and Administration Site Conditions |  | fever | 4 (8%) | –
General Disorders and Administration Site Conditions |  | weakness | 2 (4%) | 2 (12%)
General Disorders and Administration Site Conditions |  | fatigue | 7 (14%) | –
General Disorders and Administration Site Conditions |  | peripheral (edema) | 3 (6%) | 1 (6%)
General Disorders and Administration Site Conditions |  | chest pain | – | 1 (6%)
Metabolism and Nutrition Disorders |  | anorexia | 4 (8%) | –
Musculoskeletal and Connective Tissue Disorders |  | arthralgia | – | 2 (12%)
Renal and Urinary Disorders |  | proteinuria | 5 (10%) | 1 (6%)
Renal and Urinary Disorders |  | impotence | – | 1 (6%)
Respiratory, Thoracic and Mediastinal Disorders |  | cough | – | 1 (6%)
Skin and Subcutaneous Tissue Disorders |  | rash | 7 (14%) | 2 (12%)
Skin and Subcutaneous Tissue Disorders |  | ecchymosis | 3 (6%) | –
Skin and Subcutaneous Tissue Disorders |  | pruritus | 2 (4%) | 1 (6%)
Skin and Subcutaneous Tissue Disorders |  | urticaria | 4 (8%) | –
Skin and Subcutaneous Tissue Disorders |  | skin wrinkling | 3 (6%) | 1 (6%)

Taste Disturbance
A reduction in taste perception may develop. It is believed to be the result of chelation of trace metals by tiopronin. Hypogeusia is often self-limited.

6.2 Postmarketing Experience

Adverse reactions have been reported from the literature, as well as during post-approval use of THIOLA. Because the post-approval reactions are reported voluntarily from a population of uncertain size, it is not always possible to reliably estimate their frequency or establish a causal relationship to THIOLA exposure.

Adverse reactions reported during the postmarketing use of THIOLA are listed by body system in Table 2.

Table 2: | Adverse Reactions Reported for THIOLA Pharmacovigilance by System Organ Class and Preferred Term
System Organ Class |  | Preferred Term
Cardiac Disorders |  | congestive heart failure
Ear and Labyrinth Disorder |  | vertigo
Gastrointestinal Disorders |  | abdominal discomfort; abdominal distension; abdominal pain; chapped lips; diarrhea; dry mouth; dyspepsia; eructation; flatulence; gastrointestinal disorder; gastroesophageal reflux disease; nausea; vomiting; jaundice; liver transaminitis
General Disorders and Administration Site Conditions |  | asthenia; chest pain; fatigue; malaise; pain; peripheral swelling; pyrexia; swelling
Investigations |  | glomerular filtration rate decreased; weight increased
Metabolism and Nutrition Disorders |  | decreased appetite; dehydration; hypophagia
Musculoskeletal and Connective Tissue Disorders |  | arthralgia; back pain; flank pain; joint swelling; limb discomfort; musculoskeletal discomfort; myalgia; neck pain; pain in extremity
Nervous System Disorders |  | ageusia; burning sensation; dizziness; dysgeusia; headache; hypoesthesia
Renal and Urinary Disorders |  | nephrotic syndrome; proteinuria; renal failure
Skin and Subcutaneous Tissue Disorders |  | dry skin; hyperhidrosis; pemphigus foliaceus; pruritus; rash; rash pruritic; skin irritation; skin texture abnormal; skin wrinkling; urticaria

7 DRUG INTERACTIONS

7.1 Alcohol

Tiopronin is released faster from THIOLA EC in the presence of alcohol and the risk for adverse events associated with THIOLA EC when taken with alcohol is unknown. Avoid alcohol consumption 2 hours before and 3 hours after taking THIOLA EC [see Clinical Pharmacology (12.3)] .

8 USE IN SPECIFIC POPULATIONS

8.1 Pregnancy

Risk Summary
Available published case report data with tiopronin have not identified a drug-associated risk for major birth defects, miscarriage, or adverse maternal or fetal outcomes. Renal stones in pregnancy may result in adverse pregnancy outcomes (see Clinical Considerations) . In animal reproduction studies, there were no adverse developmental outcomes with oral administration of tiopronin to pregnant mice and rats during organogenesis at doses up to 2 times a 2 grams/day human dose (based on mg/m^2). The estimated background risk of major birth defects and miscarriage for the indicated population is unknown. All pregnancies have a background risk of birth defect, loss, or other adverse outcomes. In the U.S. general population, the estimated background risk of major birth defects and miscarriage in clinically recognized pregnancies are 2% to 4% and 15% to 20%, respectively.

Clinical Considerations
Disease-associated maternal and/or embryo/fetal risk
Renal stones in pregnancy may increase the risk of adverse pregnancy outcomes, such as preterm birth and low birth weight.

Data
Animal Data
No findings of fetal malformations could be attributed to the drug in reproduction studies in mice and rats at doses up to 2 times the highest recommended human dose of 2 grams/day (based on mg/m^2).

8.2 Lactation

Risk Summary
There are no data on the presence of tiopronin in either human or animal milk or on the effects of the breastfed child. A published study suggests that tiopronin may suppress milk production. Because of the potential for serious adverse reactions, including nephrotic syndrome, advise patients that breastfeeding is not recommended during treatment with THIOLA EC.

8.4 Pediatric Use

THIOLA EC is indicated in pediatric patients weighing 20 kg or more with severe homozygous cystinuria, in combination with high fluid intake, alkali, and diet modification, for the prevention of cystine stone formation who are not responsive to these measures alone. This indication is based on safety and efficacy data from a trial in patients 9 years to 68 years of age and clinical experience. Proteinuria, including nephrotic syndrome, has been reported in pediatric patients. Pediatric patients receiving greater than 50 mg/kg tiopronin per day may be at greater risk [see Dosage and Administration (2.1, 2.3), Warnings and Precautions (5.1) and Adverse Reactions (6.1)] .

THIOLA EC tablets are not approved for use in pediatric patients weighing less than 20 kg [see Dosage and Administration (2.1)] .

8.5 Geriatric Use

This drug is known to be substantially excreted by the kidney, and the risk of adverse reactions to this drug may be greater in patients with impaired renal function. Because elderly patients are more likely to have decreased renal function, care should be taken in dose selection, and it may be useful to monitor renal function.

10 OVERDOSAGE

There is no information on overdosage with tiopronin.

11 DESCRIPTION

THIOLA EC (tiopronin) delayed-release tablets are a reducing and cystine-binding thiol drug (CBTD) for oral use. Tiopronin is N‑(2‑Mercaptopropionyl) glycine and has the following structure:

Tiopronin has the empirical formula C5H9NO3S and a molecular weight of 163.20. In this drug product tiopronin exists as a dl racemic mixture.

Tiopronin is a white crystalline powder, which is freely soluble in water.

Each THIOLA EC tablet contains 100 or 300 mg of tiopronin. The inactive ingredients in THIOLA EC tablets include lactose monohydrate, hydroxypropyl cellulose, hydroxypropyl cellulose (low substitute), magnesium stearate, hydroxypropyl methylcellulose E5, methacrylic acid: ethyl acrylate copolymer (Eudragit L 100-55), talc, triethyl citrate.

12 CLINICAL PHARMACOLOGY

12.1 Mechanism of Action

The goal of therapy is to reduce urinary cystine concentration below its solubility limit. Tiopronin is an active reducing agent which undergoes thiol-disulfide exchange with cystine to form a mixed disulfide of tiopronin-cysteine. From this reaction, a water-soluble mixed disulfide is formed and the amount of sparingly soluble cystine is reduced.

12.2 Pharmacodynamics

The decrement in urinary cystine produced by tiopronin is generally proportional to the dose. A reduction in urinary cystine of 250-350 mg/day at tiopronin dosage of 1 g/day, and a decline of approximately 500 mg/day at a dosage of 2 g/day, might be expected. Tiopronin has a rapid onset and offset of action, showing a fall in cystine excretion on the first day of administration and a rise on the first day of drug withdrawal.

12.3 Pharmacokinetics

Absorption
THIOLA EC Tablets
When THIOLA IR and THIOLA EC single doses were given to fasted healthy subjects, the median time to peak plasma levels (Tmax) was 1 (range: 0.5 to 2.1) and 3 (range: 1.0 to 6.0) hours, respectively. The peak exposure (Cmax) and total exposure (AUC0-t) of tiopronin from THIOLA EC tablets were decreased by 22% and 7% respectively compared to THIOLA IR tablets.

When THIOLA EC tablets were administered crushed in applesauce, the median time to peak plasma levels of tiopronin (Tmax) was 1 hour (range: 0.5 to 2.0) compared to 3.1 hours (range: 1.5 to 4.0) when administered as intact EC tablets.

When THIOLA EC tablets were administered crushed in applesauce, the maximum concentration (Cmax) and exposure (AUC0-t) to tiopronin were increased by 38% and 14%, respectively, compared to THIOLA EC tablets administered intact.

Food Effects
Administration of the THIOLA EC tablet with food decreases Cmaxof tiopronin by 13% and AUC0-tby 25% compared to THIOLA EC administered in a fasted state.

Since the drug is dosed to effect, the study results support administration of THIOLA EC tablets with or without food; administer at the same time each day with a routine pattern with regard to meals.

Elimination
Excretion
When tiopronin is given orally, up to 48% of dose appears in urine during the first 4 hours and up to 78% by 72 hours.

Drug Interactions
Alcohol
An in vitrodissolution study was conducted to evaluate the impact of alcohol (5, 10, 20, and 40%) on the dose dumping of THIOLA EC tablets. The study results showed that the addition of alcohol to the dissolution media increases the dissolution rate of THIOLA EC tablets in the acidic media of 0.1N HCl [see Drug Interactions (7.1)] .

13 NONCLINICAL TOXICOLOGY

13.1 Carcinogenesis, Mutagenesis, Impairment of Fertility

Carcinogenesis
Long-term carcinogenicity studies in animals have not been performed.

Mutagenesis
Tiopronin was not genotoxic in the chromosomal aberration, sister chromatid exchange, and in vivomicronucleus assays.

Impairment of Fertility
High doses of tiopronin in experimental animals have been shown to interfere with maintenance of pregnancy and viability of the fetus. In 2 published male fertility studies in rats, tiopronin at 20 mg/kg/day intramuscular (IM) for 60 days induced reductions in testis, epididymis, vas deferens, and accessory sex glands weights and in the count and motility of cauda epididymal sperm.

16 HOW SUPPLIED/STORAGE AND HANDLING

100 mg delayed-release, round, white to off-white tablet imprinted with “T1” on one side with red ink and blank on the other side: Bottles of 300 NDC0178-0902-01.

300 mg delayed-release, round, white to off-white tablet imprinted with “T3” on one side with red ink and blank on the other side: Bottles of 90 NDC0178-0901-90.

Store at 25°C (77°F); excursions permitted to 15-30°C (59-86°F) [see USP Controlled Room Temperature].

17 PATIENT COUNSELING INFORMATION

Administration Instructions
For patients who cannot swallow the tablet whole, the THIOLA EC tablets can be crushed and mixed with applesauce. See Dosage and Administration (2.2) for preparation and administration instructions.

Lactation
Advise women that breastfeeding is not recommended during treatment with THIOLA EC [see Use in Specific Populations (8.2)] .

Manufactured and packaged by Mission Pharmacal Company, San Antonio, TX 78230 1355
Distributed by Travere Therapeutics, Inc., San Diego, CA 92130

Copyright© 2024 Mission Pharmacal Company.
All rights reserved.

L090201R0824

THL_T13768R0924

PACKAGE LABEL

Thiola EC®
NDC: 0178-0902-01

Thiola EC®
NDC: 0178-0901-90